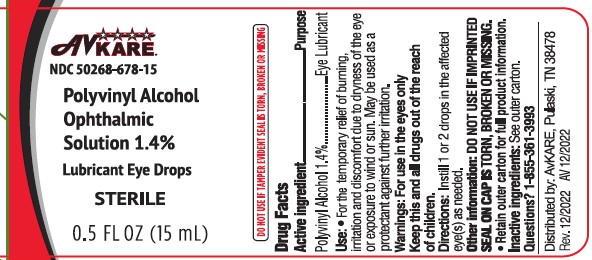 DRUG LABEL: Polyvinyl Alcohol
NDC: 50268-678 | Form: SOLUTION/ DROPS
Manufacturer: AvPAK
Category: otc | Type: HUMAN OTC DRUG LABEL
Date: 20250421

ACTIVE INGREDIENTS: POLYVINYL ALCOHOL 14 mg/1 mL
INACTIVE INGREDIENTS: EDETATE DISODIUM; SODIUM PHOSPHATE, MONOBASIC; SODIUM CHLORIDE; WATER; BENZALKONIUM CHLORIDE; SODIUM PHOSPHATE, DIBASIC

Polyvinyl Alcohol Ophthalmic Solution

Active ingredient

Polyvinyl Alcohol 1.4%

Purpose

Lubricant

Uses

- for the temporary relief of burning, irritation and discomfort due to dryness of the eye or exposure to wind or sun
- may be used as a protectant against further irritation

Warnings

- Do not use if solution changes color or becomes cloudy

When using this product

- Avoid contamination, do not touch tip of container to any surface.
- Replace cap after use

Stop use and ask a doctor if

- you experience eye pain, changes in vision, continued redness or irritation of the eye
- the condition worsens or persists for more than 72 hours

Keep out of reach of children.

If swallowed, get medical help or contact a Poison Control Center right away (1-800-222-1222)

Directions

- Shake well before use
- instill 1 to 2 drops in the affected eye(s) as needed

Other information

- Store at room temperature 15-30C (59-86F)
- Do No Use if imprinted seal on cap is torn, broken or missing
- Discard 90 days after opening
- Retain outer carton for full product information

Inactive ingredients

dibasic sodium phosphate, edetate disodium, monobasic sodium phosphate,

purified water, sodium chloride. Phosphoric acid and/or sodium hydroxide may be added to adjust pH. PRESERVATIVE ADDED: benzalkonium chloride 0.01%

Questions ?

Call 1-855-361-3993

Distributed by:

AvKARE

Pulaski, TN 38478

www.avkare.com

Rev. 12/2022 AV 12/2022